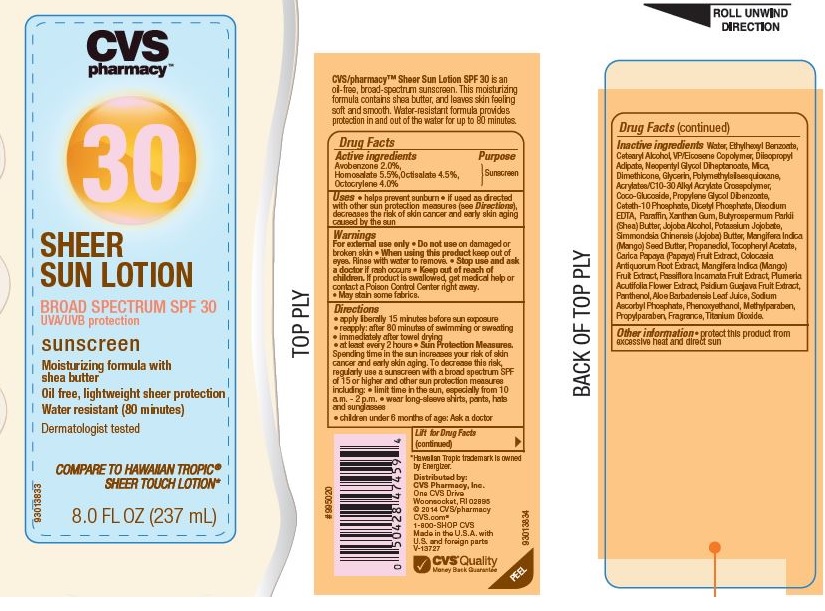 DRUG LABEL: CVS Sheer SFP 30
NDC: 59779-911 | Form: LOTION
Manufacturer: CVS Pharmacy
Category: otc | Type: HUMAN OTC DRUG LABEL
Date: 20150714

ACTIVE INGREDIENTS: AVOBENZONE 2.0 g/100 g; HOMOSALATE 5.5 g/100 g; OCTOCRYLENE 4.0 g/100 g; OCTISALATE 4.5 g/100 g
INACTIVE INGREDIENTS: WATER; 2-ETHYLHEXYL BENZOATE; CETOSTEARYL ALCOHOL; DIISOPROPYL ADIPATE; NEOPENTYL GLYCOL DIHEPTANOATE; MICA; DIMETHICONE; GLYCERIN; COCO GLUCOSIDE; PROPYLENE GLYCOL DIBENZOATE; CETETH-10 PHOSPHATE; DIHEXADECYL PHOSPHATE; EDETATE DISODIUM; PARAFFIN ; XANTHAN GUM; JOJOBA BUTTER; MANGIFERA INDICA SEED BUTTER; PROPANEDIOL; .ALPHA.-TOCOPHEROL ACETATE; PAPAYA; COLOCASIA ESCULENTA ROOT; MANGO; PASSIFLORA INCARNATA FRUIT; PLUMERIA RUBRA FLOWER; GUAVA; PANTHENOL; ALOE VERA LEAF; SODIUM ASCORBYL PHOSPHATE; PHENOXYETHANOL; METHYLPARABEN; PROPYLPARABEN; TITANIUM DIOXIDE

Drug Facts

Active ingredients

Avobenzone 2.0%, Homosalate 5.5%, Octisalate 4.5%, Octocrylene 4.0%

Purpose

Sunscreen

Uses

- helps prevent sunburn
- if used as directed with other sun protection measures (see Directions), decreases the risk of skin cancer and early skin aging caused by the sun

Warnings

For external use only

Do not use

on damaged or broken skin

When using this product

keep out of eyes. Rinse with water to remove

Stop use and ask a doctor

if rash occurs

Keep out of reach of children

If product is swallowed, get medical help or contact a Poison Control Center right away.

- May stain some fabrics

Directions

- apply liberally 15 minutes before sun exposure
- reapply; after 80 minutes of swimming or sweating
- immediately after towel drying
- at least every 2 hours
  Sun Protection Measures.Spending time in the sun increases your risk of skin cancer and early skin aging. To decrease this risk, regularly use a sunscreen with a broad spectrum SPF of 15 or higher and other sun protection measures including:

- limit time in the sun, especially from 10 a.m. - 2 p.m.
- wear long-sleeve shirts, pants, hats and sunglasses
- children under 6 months of age: Ask a doctor

Inactive ingredients

Water, Ethylhexyl Benzoate, Cetearyl Alcohol, VP/Eicosene Copolymer, Diisopropyl Adipate,Neopentyl Glycol Diheptanoate, Mica, Dimethicone, Glycerin, Polymethylsilsesquioxane, Acrylates/C10-30 Alkyl Acrylate Crosspolymer, Coco-Glucoside, Propylene Glycol Dibenzoate, Ceteth-10 Phosphate, Dicetyl Phosphate, Disodium EDTA, Paraffin, Xanthan Gum, Butyrospermum, Parkii (Shea) Butter, Jojoba Alcohol, Potassium Jojobate, Simmondsia Chinensis (Jojoba) Butter, Mangifera Indica (Mango) Seed Butter, Propanediol, Tocopheryl Acetate, Carica Papaya (Papaya) Fruit Extract, Colocasia Antiquorum Root Extract, Mangifera Indica (Mango) Fruit Extract, Passiflora Incarnata Fruit Extract, Plumeria Acutifolia Flower Extract,

Psidium Guajava Fruit Extract, Panthenol, Aloe Barbadensis Leaf Juice, Sodium Ascorbyl

Phosphate, Phenoxyethanol, Methylparaben, Propylparaben, Fragrance, Titanium Dioxide.

Other Information

- protect this product from excessive heat and direct sun

principal Display panel

NDC 59779-911-16

CVS pharmacy

30

SHEER SUN LOTION

BROAD SPECTRUM SPF 30

UVA/UVB protection

sunscreen

Moisturizing formula with shea butter

Oil free, lightweight sheer protection

Water resistant (80 minutes)

Dermatologist tested

COMPARE TO HAWAIIN TROPIC

SHEER TOUCH LOTION

8.0 FL OZ (237 mL)